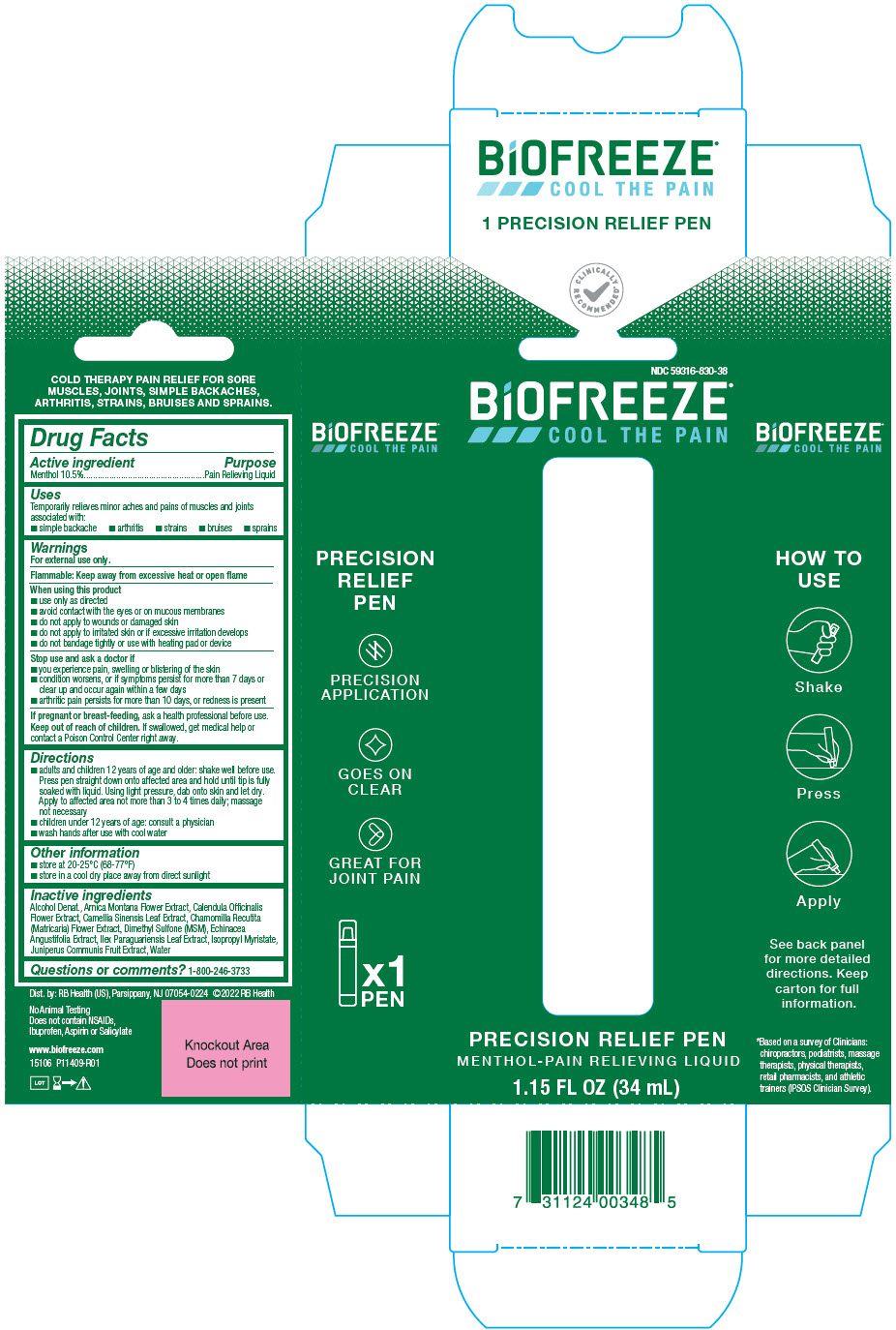 DRUG LABEL: Biofreeze Precision Relief Pen
NDC: 59316-830 | Form: LIQUID
Manufacturer: RB Health (US) LLC
Category: otc | Type: HUMAN OTC DRUG LABEL
Date: 20241227

ACTIVE INGREDIENTS: MENTHOL, UNSPECIFIED FORM 105 mg/1 mL
INACTIVE INGREDIENTS: ALCOHOL; ARNICA MONTANA FLOWER; CALENDULA OFFICINALIS FLOWER; GREEN TEA LEAF; CHAMOMILE; DIMETHYL SULFONE; ECHINACEA ANGUSTIFOLIA WHOLE; ILEX PARAGUARIENSIS LEAF; ISOPROPYL MYRISTATE; JUNIPER BERRY; WATER

Biofreeze®Precision Relief Pen

Drug Facts

Active ingredient

Menthol 10.5%

Purpose

Pain Relieving Liquid

Uses

Temporarily relieves minor aches and pains of muscles and joints associated with:

- simple backache
- arthritis
- strains
- bruises
- sprains

Warnings

For external use only.

Flammable: Keep away from excessive heat or open flame

When using this product

- use only as directed
- avoid contact with the eyes or on mucous membranes
- do not apply to wounds or damaged skin
- do not apply to irritated skin or if excessive irritation develops
- do not bandage tightly or use with heating pad or device

Stop use and ask a doctor if

- you experience pain, swelling or blistering of the skin
- condition worsens, or if symptoms persist for more than 7 days or clear up and occur again within a few days
- arthritic pain persists for more than 10 days, or redness is present

PREGNANCY OR BREAST FEEDING

If pregnant or breast-feeding,ask a health professional before use.

Keep out of reach of children.If swallowed, get medical help or contact a Poison Control Center right away.

Directions

- adults and children 12 years of age and older: shake well before use. Press pen straight down onto affected area and hold until tip is fully soaked with liquid. Using light pressure, dab onto skin and let dry. Apply to affected area not more than 3 to 4 times daily; massage not necessary
- children under 12 years of age: consult a physician
- wash hands after use with cool water

Other information

- store at 20-25°C (68-77°F)
- store in a cool dry place away from direct sunlight

Inactive ingredients

Alcohol Denat., Arnica Montana Flower Extract, Calendula Officinalis Flower Extract, Camellia Sinensis Leaf Extract, Chamomilla Recutita (Matricaria) Flower Extract, Dimethyl Sulfone (MSM), Echinacea Angustifolia Extract, Ilex Paraguariensis Leaf Extract, Isopropyl Myristate, Juniperus Communis Fruit Extract, Water

Questions or comments?

1-800-246-3733

Dist. by: RB Health (US), Parsippany, NJ 07054-0224

PRINCIPAL DISPLAY PANEL - 34 mL Bottle Carton

NDC 59316-830-38
BiOFREEZE®
COOL THE PAIN

PRECISION RELIEF PEN
MENTHOL-PAIN RELIEVING LIQUID
1.15 FL OZ (34 mL)